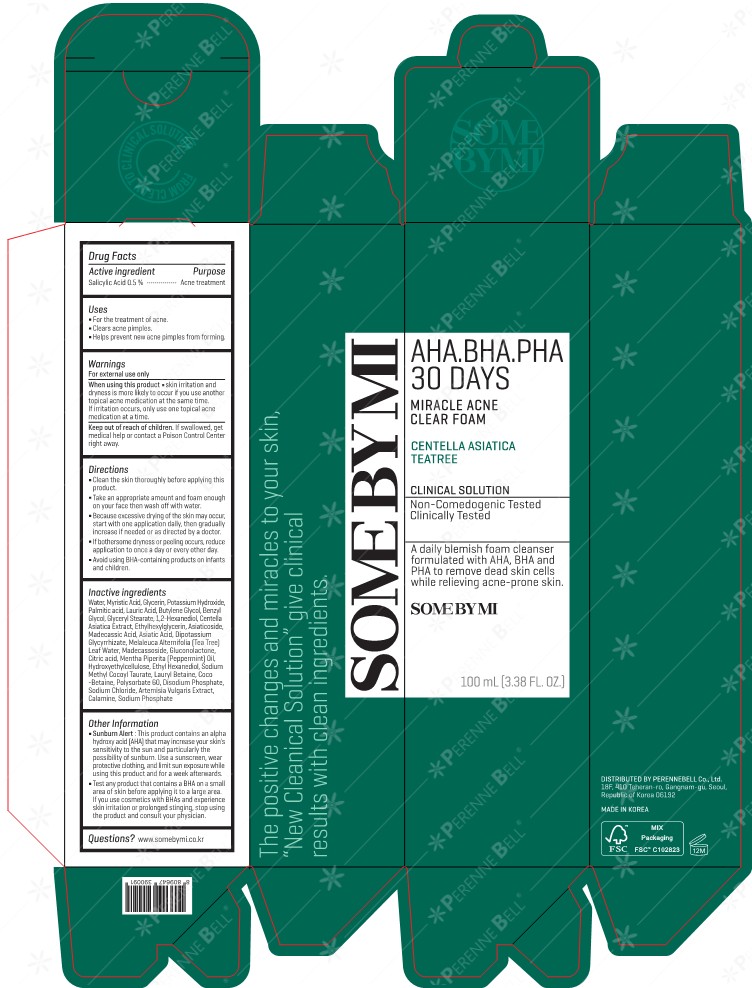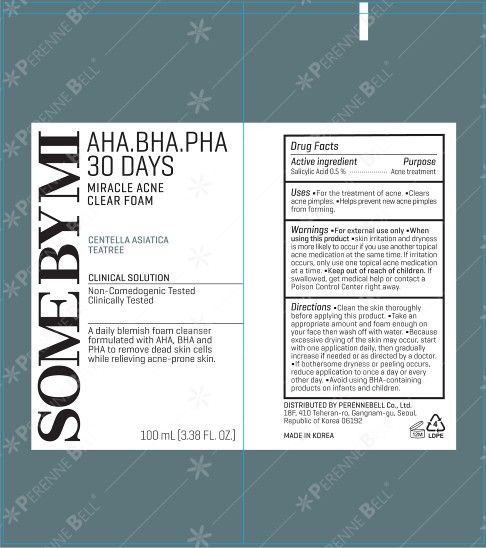 DRUG LABEL: SOME BY MI AHA BHA PHA 30 DAYS MIRACLE ACNE CLEAR FOAM
NDC: 74472-101 | Form: CREAM
Manufacturer: PERENNEBELL Co., Ltd.
Category: otc | Type: HUMAN OTC DRUG LABEL
Date: 20251016

ACTIVE INGREDIENTS: SALICYLIC ACID 0.5 g/100 g
INACTIVE INGREDIENTS: SODIUM PHOSPHATE; SODIUM METHYL COCOYL TAURATE; SODIUM CHLORIDE; ETHYLENE GLYCOL MONOBENZYL ETHER; ASIATICOSIDE; MADECASSOSIDE; CITRIC ACID MONOHYDRATE; POTASSIUM HYDROXIDE; PALMITIC ACID; GLUCONOLACTONE; LAURIC ACID; PEPPERMINT OIL; MYRISTIC ACID; 1,2-HEXANEDIOL; CENTELLA ASIATICA TRITERPENOIDS; MELALEUCA ALTERNIFOLIA (TEA TREE) LEAF OIL; GLYCYRRHIZINATE DIPOTASSIUM; GLYCERIN; BUTYLENE GLYCOL; LAURYL BETAINE; COCO-BETAINE; WATER; GLYCERYL MONOSTEARATE; ETHYLHEXYLGLYCERIN; MADECASSIC ACID; ETHOHEXADIOL; ASIATIC ACID; HYDROXYETHYL CELLULOSE, UNSPECIFIED; SODIUM PHOSPHATE, DIBASIC, ANHYDROUS

ACTIVE INGREDIENT

Salicylic Acid 0.5%

WARNINGS

For external use only

WHEN USING

When using this productskin irritation and dryness is more likely to occur if you use another topcial acne medication at the same time. If irritation occurs, only use one topical acne medication at a time.

KEEP OUT OF REACH OF CHILDREN

If swallowed, get medical help or contact a Poison Control Center right away.

INACTIVE INGREDIENT

Water, Myristic Acid, Glycerin, Potassium Hydroxide, Lauric Acid, Palmitic acid, Butylene Glycol, Stearic Acid, Sodium Methyl Cocoyl Taurate, Lauryl Betaine, Benzyl Glycol, Cetearyl Glucoside, Sorbitan Olivate, Sodium Chloride, Coco-Betaine, Glyceryl Stearate, 1,2-Hexanediol, Centella Asiatica Extract, Ethylhexylglycerin, Asiaticoside, Madecassic Acid, Asiatic Acid, Melaleuca Alternifolia (Tea Tree] Leaf Water, Mentha Piperita [Peppermint] Oil, Cetearyl Alcohol, Ethyl Hexanediol, Dipotassium Glycyrrhizate, Madecassoside, Gluconolactone, Citric acid, Artemisia Vulgaris Extract, Calamine

DOSAGE & ADMINISTRATION

INDICATIONS AND USAGE

■ For the treatment of acne

■ Clears acne pimples

■ Helps prevent new acne pimples from forming.

PURPOSE

Acne treatment

INSTRUCTIONS FOR USE

■Clean the skin thoroughly before applying this product.
■Take an appropriate amount and foam enough on your face then wash off with water.
■Because excessive drying of the skin may occur, start with one application daily, then gradually increase if needed or as directed by a doctor.

■If bothersome dryness or peeling occurs, reduce application to once a day or every other day.

■ Avoid using BHA-containing products on infants and children.

Other Information

■ Sunburn Alert: This product contains an alpha hydroxy acid [AHA] that may increase your skin's sensitivity to the sun and particularly the possibility of sunburn. Use a sunscreen, wear protective clothing, and limit sun exposure while using this product and for a week afterwards.

■ Test any product that contains a BHA on a small area of skin before applying it to a large area. If you use cosmetics with BHAS and experience skin irritation or prolonged stinging, stop using the product and consult your physician.